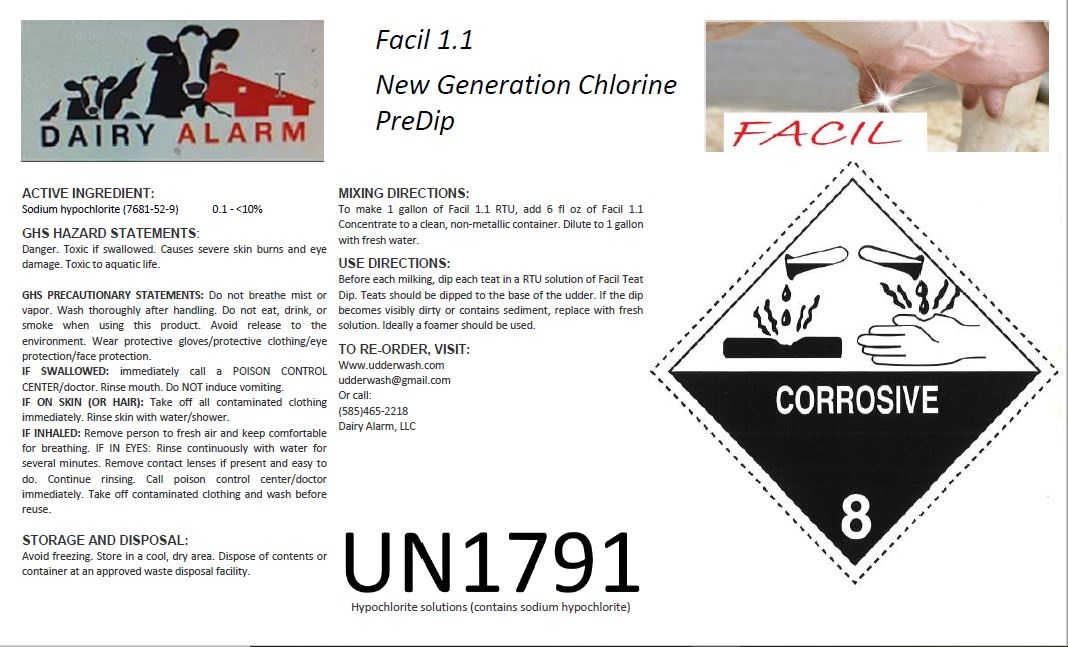 DRUG LABEL: Facil 1.1 Concentrate
NDC: 86112-1821 | Form: LIQUID
Manufacturer: Dairy Alarm LLC
Category: animal | Type: OTC ANIMAL DRUG LABEL
Date: 20191106

ACTIVE INGREDIENTS: SODIUM HYPOCHLORITE 1 kg/1 kg; POTASSIUM HYDROXIDE 1 kg/1 kg; SODIUM TRIPOLYPHOSPHATE 1 kg/1 kg; LACTIC ACID 1 kg/1 kg; SODIUM CHLORITE 1 kg/1 kg; POVIDONE 1 kg/1 kg

Facil 1.1 Concentrate SPL SubmissionDairy Alarm LLC
Dairy Alarm LLC

SAFETY DATA SHEET (Abbreviated. For full version, please contact the manufacturer or visit www.udderwash.com)

1. Identification

Product identifier Facil 1.1 Concentrate

Manufacturer

Dairy Alarm, LLC

37 Homer Street

Union Springs, NY 13160

Website: www.udderwash.com

Telephone 315-515-9698

Emergency phone number 565-465-2218

Reorder: www.udderwash.com or call company at number provided

2. Mixing and Use Directions

Add 6 fluid ounces of Facil 1.1 concentrate to a non-metallic container and dilute with clean water to 1 gallon.

Prior to milking, dip each teat into the mixed solution. Teats should be dipped to the base of the udder. If, or when, the solution becomes visibly dirty or sediment begins to build in the mixture, replace with a fresh batch of new solution mixed as previously described. If possible, a foamer should be used for application to teats.

3. Hazard(s) identification

Hazard statement Toxic if swallowed. Causes severe skin burns and eye damage. Causes serious eye damage.

Toxic to aquatic life.

Precautionary statement

Prevention Do not breathe mist or vapor. Wash thoroughly after handling. Do not eat, drink or smoke when

using this product. Avoid release to the environment. Wear protective gloves/protective

clothing/eye protection/face protection.

Response If swallowed: Immediately call a poison center/doctor. If swallowed: Rinse mouth. Do NOT induce

vomiting. If on skin (or hair): Take off immediately all contaminated clothing. Rinse skin with

water/shower. If inhaled: Remove person to fresh air and keep comfortable for breathing. If in

eyes: Rinse cautiously with water for several minutes. Remove contact lenses, if present and easy

to do. Continue rinsing. Immediately call a poison center/doctor. Wash contaminated clothing

before reuse.

Storage Store locked up.

Disposal Dispose of contents/container in accordance with local/regional/national/international regulations.

4. First-aid measures

Inhalation Move to fresh air.

Take off immediately all contaminated clothing. Rinse skin with water/shower. Call a physician or

poison control center immediately. Chemical burns must be treated by a physician. Wash

contaminated clothing before reuse.

Skin contact

Immediately flush eyes with plenty of water for at least 15 minutes. Remove contact lenses, if

present and easy to do. Continue rinsing. Call a physician or poison control center immediately.

Eye contact

Call a physician or poison control center immediately. Rinse mouth. Do not induce vomiting. If

vomiting occurs, keep head low so that stomach content doesn't get into the lungs. Do not use

mouth-to-mouth method if victim ingested the substance. Induce artificial respiration with the aid of

a pocket mask equipped with a one-way valve or other proper respiratory medical device.

Ingestion

Burning pain and severe corrosive skin damage. Causes serious eye damage. Symptoms may

include stinging, tearing, redness, swelling, and blurred vision. Permanent eye damage including

blindness could result.

Most important

symptoms/effects, acute and

delayed

Provide general supportive measures and treat symptomatically. Chemical burns: Flush with water

immediately. While flushing, remove clothes which do not adhere to affected area. Call an

ambulance. Continue flushing during transport to hospital. Keep victim warm. Keep victim under

observation. Symptoms may be delayed.

5. Handling and storage

Provide adequate ventilation. Do not breathe mist or vapor. Do not get in eyes, on skin, or on

clothing. Avoid prolonged exposure. Do not taste or swallow. When using, do not eat, drink or

smoke. Wear appropriate personal protective equipment. Wash hands thoroughly after handling.

Avoid release to the environment.

Precautions for safe handling

Store locked up. Store in original tightly closed container. Store away from incompatible materials

(see Section 10 of the SDS).